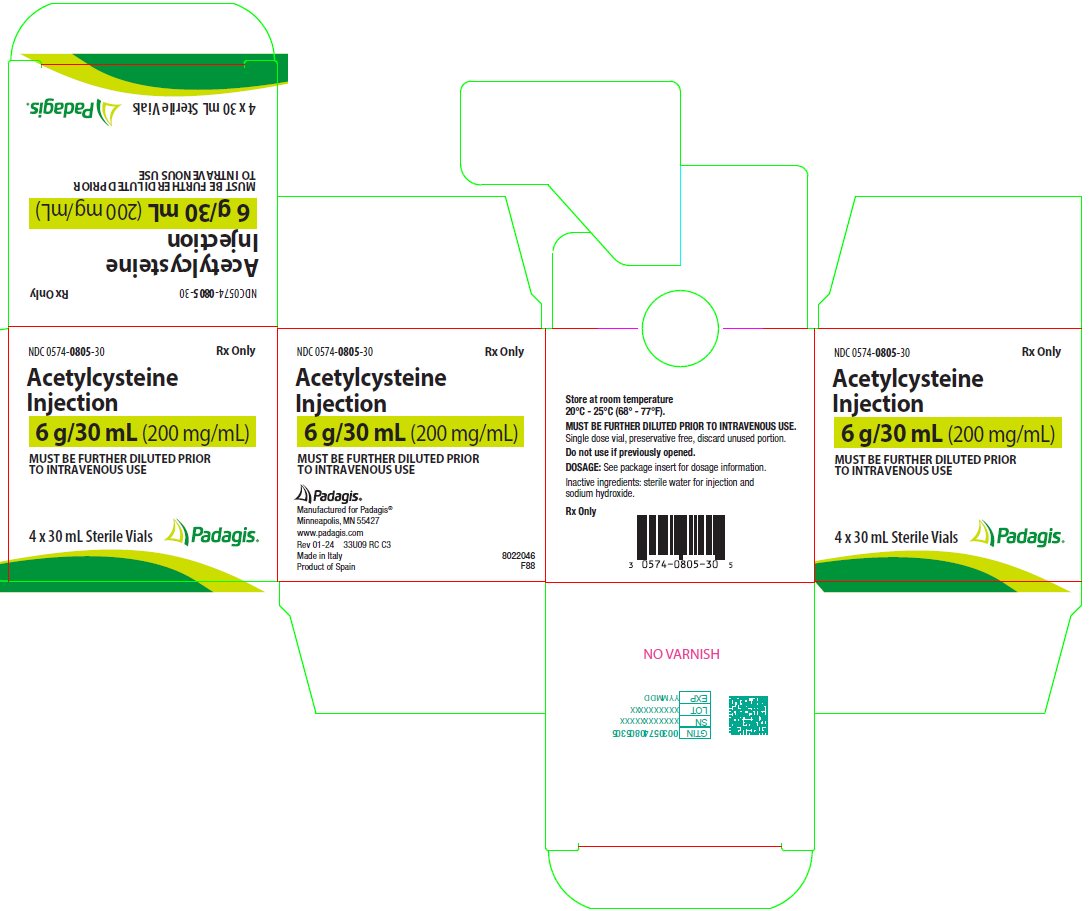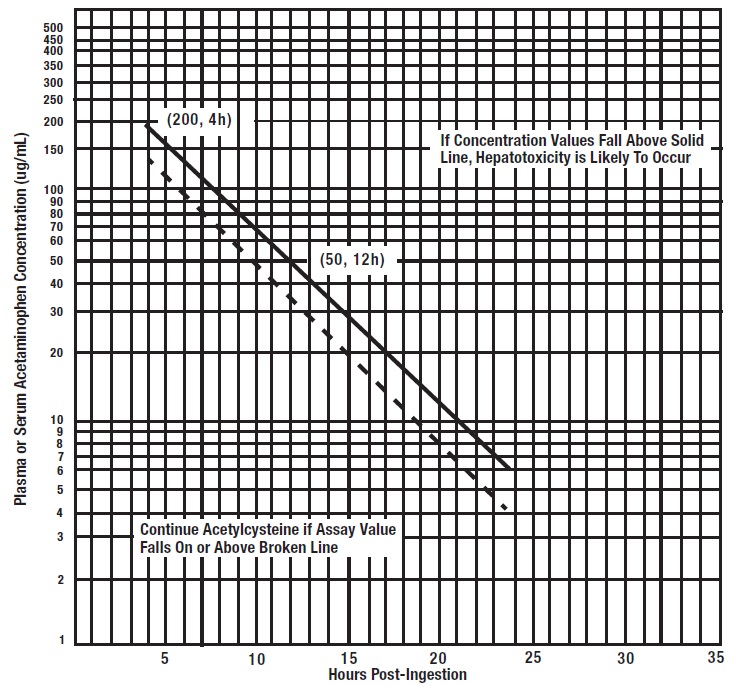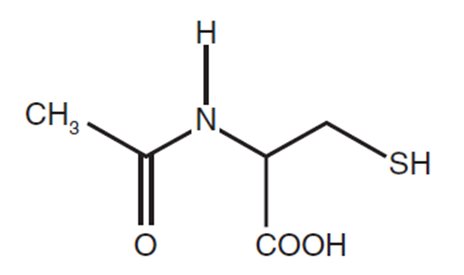 DRUG LABEL: acetylcysteine
NDC: 0574-0805 | Form: INJECTION
Manufacturer: Padagis US LLC
Category: prescription | Type: HUMAN PRESCRIPTION DRUG LABEL
Date: 20240131

ACTIVE INGREDIENTS: ACETYLCYSTEINE 200 mg/1 mL
INACTIVE INGREDIENTS: SODIUM HYDROXIDE; WATER

HIGHLIGHTS OF PRESCRIBING INFORMATION

These highlights do not include all the information needed to use ACETYLCYSTEINE INJECTION safely and effectively. See full prescribing information for ACETYLCYSTEINE INJECTION.
ACETYLCYSTEINE INJECTION, for intravenous use
Initial U.S. Approval: 2004

1 INDICATIONS AND USAGE

Acetylcysteine injection is an antidote for acetaminophen overdose indicated to prevent or lessen hepatic injury after ingestion of a potentially hepatotoxic quantity of acetaminophen in patients with an acute ingestion or from repeated supratherapeutic ingestion (RSI) (1).

2 DOSAGE AND ADMINISTRATION

Pre-Treatment Assessment Following Acute Ingestion (2.1):

Obtain a plasma or serum sample to assay for acetaminophen concentration at least 4 hours after ingestion.

- If the time of acetaminophen ingestion is unknown:
  - Administer a loading dose of acetylcysteine injection immediately.
  - Obtain an acetaminophen concentration to determine need for continued treatment.
- If the acetaminophen concentration cannot be obtained (or is unavailable or uninterpretable) within the 8-hour time interval after acetaminophen ingestion or there is clinical evidence of acetaminophen toxicity:
  - Administer a loading dose of acetylcysteine injection immediately and continue treatment for a total of three doses over 21 hours.
- If the patient presents more than 8 hours after ingestion and the time of acute acetaminophen ingestion is known:
  - Administer a loading dose of acetylcysteine injection immediately.
  - Obtain acetaminophen concentration to determine need for continued treatment.
- If the patient presents less than 8 hours after ingestion and the time of acute acetaminophen ingestion is known and the acetaminophen concentration is known:
  - Use the Rumack-Matthew nomogram (Figure 1) to determine whether or not to initiate treatment with acetylcysteine injection (2.2)

Nomogram for Estimating Potential for Hepatotoxicity from Acute Acetaminophen Ingestion (2.2):

- See Full Prescribing Information for instructions on how to use the nomogram to determine the need for dosing.

Preparation and Storage of Diluted Solution Prior to Administration (2.3):

Acetylcysteine injection is hyperosmolar (2600 mOsmol/L), therefore acetylcysteine injection must be diluted in sterile water for injection, 0.45% sodium chloride injection, or 5% dextrose in water injection prior to intravenous administration. See Full Prescribing Information for examples of osmolarity depending on the type of solution and ACETADOTE concentration.

Recommended Adult and Pediatric Dosage (2.4):

- Acetylcysteine injection is for intravenous administration only
- Total dosage of acetylcysteine injection is 300 mg/kg given intravenously as 3 separate doses and total recommended infusion time for 3 doses is 21 hours
- See Full Prescribing Information for weight-based dosage and weight-based dilution (2.4)
- See Full Prescribing Information for recommendations for continuing acetylcysteine injection treatment after 21 hours (2.2)

Repeated Supratherapeutic Acetaminophen Ingestion (2.5):

- Obtain acetaminophen concentration and other laboratory tests to guide treatment; Rumack-Matthew nomogram does not apply.

3 DOSAGE FORMS AND STRENGTHS

Injection: 6 grams/30 mL (200 mg/mL) in a single-dose vial (3)

4 CONTRAINDICATIONS

Patients with a previous hypersensitivity reaction to acetylcysteine (4)

5 WARNINGS AND PRECAUTIONS

- Hypersensitivity Reactions, Including Hypotension, Wheezing, Shortness of Breath and Bronchospasm: Observe patients during and after the infusion; immediately discontinue infusion if a serious reaction occurs and initiate appropriate treatment. Acetylcysteine injection infusion may be carefully restarted after treatment of hypersensitivity has been initiated (5.1).
- Fluid Overload: Total volume administered should be reduced for patients weighing less than 40 kg and for those requiring fluid restriction (5.2).

6 ADVERSE REACTIONS

Most common adverse reactions (> 2%) are rash, urticaria/facial flushing and pruritus (6.1).

To report SUSPECTED ADVERSE REACTIONS, contact Padagis® at 1-866-634-9120 or FDA at 1-800-FDA-1088 or www.fda.gov/medwatch.

FULL PRESCRIBING INFORMATION

1 INDICATIONS AND USAGE

Acetylcysteine injection is indicated to prevent or lessen hepatic injury after ingestion of a potentially hepatotoxic quantity of acetaminophen in patients with acute ingestion or from repeated supratherapeutic ingestion (RSI).

2 DOSAGE AND ADMINISTRATION

2.1 Pre-Treatment Assessment and Testing Following Acute Acetaminophen Ingestion

The following recommendations are related to acute acetaminophen ingestion. For recommendations related to repeated supratherapeutic exposure see Dosage and Administration (2.5).

1. Assess the history and timing of acetaminophen ingestion as an overdose.

- The reported history of the quantity of acetaminophen ingested as an overdose is often inaccurate and is not a reliable guide to therapy.

2. Obtain the following laboratory tests to monitor hepatic and renal function and electrolyte and fluid balance: aspartate aminotransferase (AST), alanine aminotransferase (ALT), bilirubin, international normalized ratio (INR), creatinine, blood urea nitrogen (BUN), blood glucose, and electrolytes.

3. Obtain a plasma or serum sample to assay for acetaminophen concentration at least 4 hours after ingestion. Acetaminophen concentrations obtained earlier than 4 hours post-ingestion may be misleading as they may not represent maximum acetaminophen concentrations.

4. If the time of acute acetaminophen ingestion is unknown:

- Administer a loading dose of acetylcysteine injection immediately [see Dosage and Administration (2.4)].
- Obtain an acetaminophen concentration to determine need for continued treatment [see Dosage and Administration (2.2)].

5. If the acetaminophen concentration cannot be obtained (or is unavailable or uninterpretable) within the 8-hour time interval after acetaminophen ingestion or there is clinical evidence of acetaminophen toxicity:

- Administer a loading dose of acetylcysteine injection immediately and continue treatment for a total of three doses over 21 hours [see Dosage and Administration (2.4)].

6. If the patient presents more than 8 hours after ingestion and the time of acute acetaminophen ingestion is known:

- Administer a loading dose of acetylcysteine injection immediately [see Dosage and Administration (2.4)]
- Obtain an acetaminophen concentration to determine need for continued treatment [see Dosage and Administration (2.2)].

7. If the patient presents less than 8 hours after ingestion and the time of acute acetaminophen ingestion is known and the acetaminophen concentration is known:

- Use the Rumack-Matthew nomogram (Figure 1) to determine whether or not to initiate treatment with acetylcysteine injection [see Dosage and Administration (2.2)].

2.2 Nomogram for Estimating Potential for Hepatotoxicity from Acute Acetaminophen Ingestion and Need for Acetylcysteine Injection Treatment

Acetylcysteine injection is an antidote for acetaminophen overdose. The critical ingestion-treatment interval for maximal protection against severe hepatic injury is between 0 – 8 hours. Efficacy diminishes progressively after 8 hours and treatment initiation between 15 and 24 hours post-ingestion of acetaminophen yields limited efficacy. However, it does not appear to worsen the condition of patients and it should not be withheld, since the reported time of ingestion may not be correct.

If the timing of the acute acetaminophen ingestion is known and the results of the acetaminophen assay are available within 8 hours:

- Refer to the Rumack-Matthew nomogram (see Figure 1) to determine whether or not to initiate treatment with acetylcysteine injection.
- Initiation of acetylcysteine injection depends on the plasma or serum acetaminophen concentration and also the clinical presentation of the patient.

The nomogram may underestimate the hepatotoxicity risk in patients with chronic alcoholism, malnutrition, or CYP2E1 enzyme inducing drugs (e.g., isoniazid), and consideration should be given to treating these patients even if the acetaminophen concentrations are in the nontoxic range.

Loading dose

For patients whose acetaminophen concentrations are at or above the “possible” toxicity line (dotted line in nomogram):

- Administer a loading dose of acetylcysteine injection [see Dosage and Administration (2.4)].

For patients with an acute overdose from an extended-release acetaminophen, if the acetaminophen concentration at 4 hours post ingestion is below the possible toxicity line then obtain a second sample for acetaminophen concentration 8 to 10 hours after the acute ingestion. If the second value is at or above the “possible” toxicity line (dotted line in nomogram):

- Administer a loading dose of acetylcysteine injection [see Dosage and Administration (2.4)].

For patients whose values are below the “possible” toxicity line, but time of ingestion was unknown or sample was obtained less than 4 hours after ingestion:

- Administer a loading dose of acetylcysteine injection [see Dosage and Administration (2.4)].

For patients whose values are below the “possible” toxicity line and time of ingestion is known and the sample was obtained more than 4 hours after ingestion, do not administer acetylcysteine injection because there is minimal risk of hepatotoxicity.

Figure 1. Rumack-Matthew Nomogram for Estimating Potential for Hepatoxicity for Acetaminophen Poisoning – Plasma or Serum Acetaminophen Concentration versus Time (hours) Post-acetaminophen Ingestion

(Adapted from Rumack and Matthew, Pediatrics 1975; 55: 871-876)

Maintenance Dose

Determine need for continued treatment with acetylcysteine injection after the loading dose. Choose ONE of the following based on the acetaminophen concentration:

The acetaminophen concentration is above the possible toxicity line according to the nomogram (see Figure 1):

- Continue acetylcysteine injection treatment with the maintenance dose for a total of three separate doses over an infusion period of 21 hours [see Dosage and Administration (2.4)].
- Monitor hepatic and renal function and electrolytes throughout treatment.

The acetaminophen concentration could not be obtained:

- Continue acetylcysteine injection treatment with the maintenance dose for a total of three separate doses over an infusion period of 21 hours [see Dosage and Administration (2.4)].
- Monitor hepatic and renal function and electrolytes throughout treatment.

For patients whose acetaminophen concentration is below the “possible” toxicity line (see Figure 1) and time of ingestion is known and the sample was obtained more than 4 hours after ingestion:

- Discontinue acetylcysteine injection.

The acetaminophen concentration was in the non-toxic range, but time of ingestion was unknown or less than 4 hours:

- Obtain a second sample for acetaminophen concentration and consider the patient’s clinical status to decide whether or not to continue acetylcysteine injection treatment.
- If there is any uncertainty as to patient’s risk of developing hepatotoxicity, it is recommended to administer a complete treatment course.

Continued Therapy After Completion of Loading and Maintenance Doses

In cases of suspected massive overdose, or with concomitant ingestion of other substances, or in patients with preexisting liver disease; the absorption and/or the half-life of acetaminophen may be prolonged. In such cases, consideration should be given to the need for continued treatment with acetylcysteine injection beyond a total of three separate doses over a 21-hour infusion period.

Acetaminophen levels and ALT/AST and INR should be checked after the last maintenance dose. If acetaminophen levels are still detectable, or if the ALT/AST are still increasing or the INR remains elevated; dosing should be continued and the treating physician should contact a US regional poison center at 1-800-222-1222, alternatively, a “special health professional assistance line for acetaminophen overdose” at 1-800-525-6115 for assistance with dosing recommendations, or 1-877-484-2700 for additional information.

2.3 Preparation and Storage of Acetylcysteine Injection Diluted Solution Prior to Administration

Because acetylcysteine injection is hyperosmolar (2600 mOsmol/L), acetylcysteine injection must be diluted in sterile water for injection, 0.45% sodium chloride injection (1/2 normal saline), or 5% dextrose in water prior to intravenous administration [see Warnings and Precautions (5.2)]. Dilution in these three solutions results in different osmolarity of the solution for intravenous administration (see Table 1 for examples of different osmolarity of the solution depending on the type of solution and the acetylcysteine injection concentration).

Visually inspect for particular matter and discoloration prior to administration. The color of the diluted solution ranges from colorless to a slight pink or purple once the stopper is punctured (the color change does not affect the quality of the product). The diluted solution can be stored for 24 hours at room temperature. Discard unused portion. If a vial was previously opened, do not use for intravenous administration.

Table 1. Examples of Acetylcysteine Injection Concentration and Osmolarity in Three Solutions
Acetylcysteine Injection Concentration | Osmolarity
Acetylcysteine Injection Concentration | Sterile Water for Injection | ½ Normal Saline | D5W
7 mg/mL | 91 mOsmol/L* | 245 mOsmol/L | 343 mOsmol/L
24 mg/mL | 312 mOsmol/L | 466 mOsmol/L | 564 mOsmol/L

* Adjust osmolarity to a physiologically safe level (generally not less than 150 mOsmol/L in pediatric patients).

2.4 Recommended Dosage in Adults and Pediatrics for Acute Acetaminophen Ingestion

Acetylcysteine Injection is for intravenous administration only.

Dosage Regimen

The total recommended dosage of acetylcysteine injection is 300 mg/kg given intravenously as 3 separate, sequential doses (i.e., 3-bag method to administer the loading, second, and third doses). The total recommended infusion time for 3 doses is 21 hours. For the recommended weight-based dosage and weight-based dilution in patients who weigh:

- 5 to 20 kg (see Table 2)
- 21 to 40 kg (see Table 3)
- 41 kg or greater (see Table 4)

Table 2. Recommended Acetylcysteine Injection Dosage and Dilution for Patients 5 kg to 20 kg
Body Weight | Bag 1 (Loading Dose); 150 mg/kg in 3 mL/kg of diluent* infused over 1 hour |  | Bag 2 (Second Dose); 50 mg/kg in 7 mL/kg of diluent* infused over 4 hours |  | Bag 3 (Third Dose); 100 mg/kg diluted in 14 mL/kg of diluent* infused over 16 hours
Body Weight | Loading Dose | Diluent Volume | Second Dose | Diluent Volume | Third Dose | Diluent Volume
5 kg** | 750 mg | 15 mL | 250 mg | 35 mL | 500 mg | 70 mL
10 kg | 1,500 mg | 30 mL | 500 mg | 70 mL | 1,000 mg | 140 mL
15 kg | 2,250 mg | 45 mL | 750 mg | 105 mL | 1,500 mg | 210 mL
20 kg | 3,000 mg | 60 mL | 1,000 mg | 140 mL | 2,000 mg | 280 mL

* Dilute acetylcysteine injection in one of the following three solutions: sterile water for injection, 0.45% sodium chloride injection, or 5% dextrose in water.

** Recommended dosing for those less than 5 kg has not been studied.

Table 3. Recommended Acetylcysteine Injection Dosage and Dilution for Patients 21 kg to 40 kg
Body Weight | Bag 1 (Loading Dose); 150 mg/kg in 100 mL of diluent* infused over 1 hour | Bag 2 (Second Dose); 50 mg/kg in 250 mL of diluent* infused over 4 hours | Bag 3 (Third Dose); 100 mg/kg in 500 mL of diluent * infused over 16 hours
21 kg | 3,150 mg | 1,050 mg | 2,100 mg
30 kg | 4,500 mg | 1,500 mg | 3,000 mg
40 kg | 6,000 mg | 2,000 mg | 4,000 mg

* Dilute acetylcysteine injection in one of the following three solutions: sterile water for injection, 0.45% sodium chloride injection, or 5% dextrose in water.

Table 4. Recommended Acetylcysteine Injection Dosage and Dilution for Patients 41 kg or Greater
Body Weight | Bag 1 (Loading Dose); 150 mg/kg in 200 mL of diluent* infused over 1 hour | Bag 2 (Second Dose); 50 mg/kg in 500 mL of diluent* infused over 4 hours | Bag 3 (Third Dose); 100 mg/kg in 1000 mL of diluent * infused over 16 hours
41 kg | 6,150 mg | 2,050 mg | 4,100 mg
50 kg | 7,500 mg | 2,500 mg | 5,000 mg
60 kg | 9,000 mg | 3,000 mg | 6,000 mg
70 kg | 10,500 mg | 3,500 mg | 7,000 mg
80 kg | 12,000 mg | 4,000 mg | 8,000 mg
90 kg | 13,500 mg | 4,500 mg | 9,000 mg
≥100 kg** | 15,000 mg | 5,000 mg | 10,000 mg

* Dilute acetylcysteine injection in one of the following three solutions: sterile water for injection, 0.45% sodium chloride injection, or 5% dextrose in water. ** No specific studies have been conducted to evaluate the necessity of dose adjustments in patients weighing over 100 kg. Limited information is available regarding the dosing requirements of patients that weigh more than 100 kg.

2.5 Recommendations for Repeated Supratherapeutic Acetaminophen Ingestion

Repeated supratherapeutic acetaminophen ingestion (RSI) is an ingestion of acetaminophen at dosages higher than those recommended for extended periods of time. The risk of hepatotoxicity and the recommendations for treatment of acute acetaminophen ingestion (i.e., the Rumack-Matthew nomogram) do not apply to patients with RSI. Therefore, obtain the following information to guide acetylcysteine injection treatment for RSI:

- Acetaminophen serum or plasma concentrations. A reported history of the quantity of acetaminophen ingested is often inaccurate and is not a reliable guide to therapy.
- Laboratory tests to monitor hepatic and renal function and electrolyte and fluid balance: AST, ALT, bilirubin, INR, creatinine, BUN, blood glucose, and electrolytes.

For specific acetylcysteine injection dosage and administration information in patients with RSI, consider contacting your regional poison center at 1-800-222-1222, or alternatively, a special health professional assistance line for acetaminophen overdose at 1-800-525-6115.

3 DOSAGE FORMS AND STRENGTHS

Injection: 200 mg/mL (6 grams of acetylcysteine in 30 mL) in a single-dose vial.

4 CONTRAINDICATIONS

Acetylcysteine injection is contraindicated in patients with a previous hypersensitivity reaction to acetylcysteine [see Warnings and Precautions (5.1)].

5 WARNINGS AND PRECAUTIONS

5.1 Hypersensitivity Reactions

Serious acute hypersensitivity reactions during acetylcysteine administration including rash, hypotension, wheezing, and/or shortness of breath, have been observed in patients receiving intravenous acetylcysteine for acetaminophen overdose and occurred soon after initiation of the infusion [see Adverse Reactions (6.1)]. If a severe hypersensitivity reaction occurs, immediately stop the infusion of acetylcysteine injection and initiate appropriate treatment.

One patient with asthma developed bronchospasm and died after intravenous administration of acetylcysteine. Acetylcysteine injection should be used with caution in patients with asthma, or where there is a history of bronchospasm. Patients with asthma should be closely monitored during initiation of acetylcysteine injection therapy and throughout acetylcysteine injection therapy.

Acute flushing and erythema of the skin may occur in patients receiving acetylcysteine intravenously. These reactions usually occur 30 to 60 minutes after initiating the infusion and often resolve spontaneously despite continued infusion of acetylcysteine. If a reaction to acetylcysteine involves more than simply flushing and erythema of the skin, it should be treated as a hypersensitivity reaction.

Management of less severe hypersensitivity reactions should be based upon the severity of the reaction and include temporary interruption of the infusion and/or administration of antihistaminic drugs. The acetylcysteine injection infusion may be carefully restarted after treatment of the hypersensitivity symptoms has been initiated; however, if the hypersensitivity reaction returns upon re-initiation of treatment or increases in severity, acetylcysteine injection should be discontinued and alternative patient management should be considered.

5.2 Fluid Overload

The total volume of acetylcysteine injection administered should be adjusted for patients less than 40 kg and for those requiring fluid restriction. To avoid fluid overload, the volume of diluent should be reduced as needed [see Dosage and Administration (2)]. If volume is not adjusted fluid overload can occur, potentially resulting in hyponatremia, seizure and death.

Intravenous administration of acetylcysteine injection can cause fluid overload, potentially resulting in hyponatremia, seizure and death. To avoid fluid overload, use the recommended dilution shown in Tables 2, 3 and 4 [see Dosage and Administration (2.4)].

6 ADVERSE REACTIONS

6.1 Clinical Studies Experience

Because clinical trials are conducted under widely varying conditions, adverse reaction rates observed in the clinical trials of a drug cannot be directly compared to rates in the clinical trials of another drug and may not reflect the rates observed in practice.

In the literature the most frequently reported adverse reactions attributed to intravenous acetylcysteine administration were rash, urticaria and pruritus. The frequency of adverse reactions has been reported to be between 0.2% and 21%, and they most commonly occur during the initial loading dose of acetylcysteine.

Loading Dose/Infusion Rate Study

In a randomized, open-label, multi-center clinical study conducted in Australia in patients with acetaminophen poisoning, the rates of hypersensitivity reactions between a 15-minute and 60-minute intravenous infusion for the 150 mg/kg loading dose of acetylcysteine were compared.

The incidence of drug-related adverse reactions occurring within the first 2 hours following acetylcysteine administration is presented in Table 5. Overall, 17% of patients developed an acute hypersensitivity reaction (18% in the 15-minute infusion group; 14% in the 60-minute infusion group) [see Warnings and Precautions (5.1), Clinical Studies (14)].

Table 5. Incidence of Drug-Related Adverse Reactions Occurring Within the First 2 Hours Following Study Drug Administration by Preferred Term: Loading Dose/Infusion Rate Study

Treatment Group | 15-minutes |  |  |  | 60-minutes
Number of Patients | n=109 |  |  |  | n=71
Cardiac disorders | 5 (5%) |  |  |  | 2 (3%)
Severity:; Tachycardia NOS | Unkn | Mild | Moderate | Severe | Unkn | Mild | Moderate | Severe
Severity:; Tachycardia NOS |  | 4 (4%) | 1 (1%) |  |  | 2 (3%)
Gastrointestinal disorders | 16 (15%) |  |  |  | 7 (10%)
Severity:; Nausea; Vomiting NOS | Unkn | Mild | Moderate | Severe | Unkn | Mild | Moderate | Severe
Severity:; Nausea; Vomiting NOS | 1 (1%) |  | 6 (6%) |  |  | 1 (1%) | 1 (1%)
Severity:; Nausea; Vomiting NOS |  | 2 (2%) | 11 (10%) |  |  | 2 (3%) | 4 (6%)
Immune System Disorders | 20 (18%) |  |  |  | 10 (14%)
Severity:; Hypersensitivity reaction | Unkn | Mild | Moderate | Severe | Unkn | Mild | Moderate | Severe
Severity:; Hypersensitivity reaction | 2 (2%) | 6 (6%) | 11 (10%) | 1 (1%) |  | 4 (6%) | 5 (7%) | 1 (1%)
Respiratory, thoracic and mediastinal disorders | 2 (2%) |  |  |  | 2 (3%)
Severity: | Unkn | Mild | Moderate | Severe | Unkn | Mild | Moderate | Severe
Pharyngitis |  |  | 1 (1%)
Rhinorrhea |  | 1 (1%)
Rhonchi |  |  |  |  |  | 1 (1%)
Throat tightness |  |  |  |  |  | 1 (1%)
Skin & subcutaneous tissue disorders | 6 (6%) |  |  |  | 5 (7%)
Severity: | Unkn | Mild | Moderate | Severe | Unkn | Mild | Moderate | Severe
Pruritus |  | 1 (1%) |  |  |  | 2 (3%)
Rash NOS |  | 3 (3%) | 2 (2%) |  |  | 3 (4%)
Vascular disorders | 2 (2%) |  |  |  | 3 (4%)
Severity: | Unkn | Mild | Moderate | Severe | Unkn | Mild | Moderate | Severe
Flushing |  | 1 (1%) | 1 (1%) |  |  | 2 (3%) | 1 (1%)

Unkn=Unknown; NOS=not otherwise specified

Safety Study

A large multi-center study was performed in Canada where data were collected from patients who were treated with intravenous acetylcysteine for acetaminophen overdose between 1980 and 2005. This study evaluated 4709 adult cases and 1905 pediatric cases. The incidence of hypersensitivity reactions in adult (overall incidence 8%) and pediatric (overall incidence 10%) patients is presented in Tables 6 and 7.

Table 6. Distribution of reported hypersensitivity reactions in adult patients receiving intravenous acetylcysteine

Reaction | Incidence (%) n=4709
Urticaria/Facial Flushing | 6.1%
Pruritus | 4.3%
Respiratory Symptoms* | 1.9%
Edema | 1.6%
Hypotension | 0.1%
Anaphylaxis | 0.1%

Table 7. Distribution of reported hypersensitivity reactions in pediatric patients receiving intravenous acetylcysteine

Reaction | Incidence (%) n=1905
Urticaria/Facial Flushing | 7.6%
Pruritus | 4.1%
Respiratory Symptoms* | 2.2%
Edema | 1.2%
Anaphylaxis | 0.2%
Hypotension | 0.1%

*Respiratory symptoms are defined as presence of any of the following: cough, wheezing, stridor, shortness of breath, chest tightness, respiratory distress, or bronchospasm.

*Respiratory symptoms are defined as presence of any of the following: cough, wheezing, stridor, shortness of breath, chest tightness, respiratory distress, or bronchospasm.

8 USE IN SPECIFIC POPULATIONS

8.1 Pregnancy

Risk Summary

Limited published case reports and case series of pregnant women exposed to acetylcysteine during various trimesters are not sufficient to inform any drug associated risk. Delaying treatment of acetaminophen overdose may increase the risk of maternal or fetal morbidity and mortality [see Clinical Considerations]. Reproduction studies in rats and rabbits following oral administration of acetylcysteine during the period of organogenesis at doses similar to the total intravenous dose (based on the body surface area) did not cause any adverse effects to the fetus. The estimated background risk of major birth defects and miscarriage for the indicated population is unknown. In the U.S. general population, the estimated background risk of major birth defects and miscarriage in clinically recognized pregnancies is 2% to 4% and 15% to 20%, respectively.

Clinical Considerations

Disease-Associated Maternal and/or Embryo/Fetal Risk

Acetaminophen and acetylcysteine cross the placenta. Delaying treatment in pregnant women with acetaminophen overdose and potentially toxic acetaminophen plasma levels may increase the risk of maternal and fetal morbidity and mortality.

Data

Animal Data

Reproduction studies have been performed following administration of acetylcysteine during the period of organogenesis in rats at oral doses up to 2000 mg/kg/day (1.1 times the recommended total human intravenous dose of 300 mg/kg based on body surface area comparison) and in rabbits at oral doses up to 1000 mg/kg/day (1.1 times the recommended total human intravenous dose of 300 mg/kg based on body surface area comparison). No adverse developmental outcomes due to acetylcysteine were observed.

8.2 Lactation

Risk Summary

There are no data on the presence of acetylcysteine in human milk, the effects on the breastfed infant, or the effects on milk production. The developmental and health benefits of breastfeeding should be considered along with the mother’s clinical need for acetylcysteine injection and any potential adverse effects on the breastfed child from acetylcysteine injection or from the underlying maternal condition.

Clinical Considerations

Based on the pharmacokinetic data, acetylcysteine should be nearly completely cleared 30 hours after administration. Breastfeeding women may consider pumping and discarding their milk for 30 hours after administration.

8.4 Pediatric Use

Safety and effectiveness of acetylcysteine injection in pediatric patients have not been established by adequate and well-controlled studies. Use of acetylcysteine injection in pediatric patients 5 kg and greater is based on clinical practice [see Dosage and Administration (2.4)].

10 OVERDOSAGE

An initial 150 mg/kg dose of acetylcysteine for a patient weighting 106 kg was mistakenly calculated as 160 g (a decimal point error resulting in a 10-fold higher than prescribed dose). An hour after the infusion started, the patient complained of generalized heat sensation and body pain and developed widespread urticaria and hypotension. The second acetylcysteine infusion was withheld and the patient was treated for anaphylaxis. Despite treatment the patient subcomed to the acute inflammatory reaction and died.

Single intravenous doses of acetylcysteine at 1000 mg/kg in mice, 2445 mg/kg in rats, 1500 mg/kg in guinea pigs, 1200 mg/kg in rabbits and 500 mg/kg in dogs were lethal. Symptoms of acute toxicity in the animals were ataxia, hypoactivity, labored respiration, cyanosis, loss of righting reflex and convulsions.

11 DESCRIPTION

Acetylcysteine injection is an intravenous antidote for the treatment of acetaminophen overdose. Acetylcysteine is the nonproprietary name for the N-acetyl derivative of the naturally occurring amino acid, L-cysteine (N-acetyl-L-cysteine,). The compound is a white crystalline powder, which melts in the range of 104° to 110°C and has a very slight odor.

The molecular formula of the compound is C5H9NO3S, and its molecular weight is 163.2. Acetylcysteine has the following structural formula:

Acetylcysteine injection is supplied as a sterile solution in vials containing 20% w/v (200 mg/mL) acetylcysteine. The pH of the solution ranges from 6.0 to 7.5. Acetylcysteine injection contains the following inactive ingredients: sodium hydroxide (used for pH adjustment), and Sterile Water for Injection, USP.

12 CLINICAL PHARMACOLOGY

12.1 Mechanism of Action

Acetylcysteine has been shown to reduce the extent of liver injury following acetaminophen overdose. Acetaminophen doses of 150 mg/kg or greater have been associated with hepatotoxicity. Acetylcysteine probably protects the liver by maintaining or restoring the glutathione levels, or by acting as an alternate substrate for conjugation with, and thus detoxification of, the reactive metabolite of acetaminophen.

12.3 Pharmacokinetics

After a single intravenous dose of acetylcysteine, the plasma concentration of total acetylcysteine declined in a poly-exponential decay manner with a mean terminal half-life (T1/2) of 5.6 hours. The mean clearance (CL) for acetylcysteine was 0.11 liter/hr/kg and renal CL constituted about 30% of the total CL.

Distribution:

The steady-state volume of distribution (Vdss) following administration of an intravenous dose of acetylcysteine was 0.47 liter/kg. The protein binding of acetylcysteine ranges from 66 to 87%.

Elimination

Metabolism:

Acetylcysteine (i.e., N-acetylcysteine) is postulated to form cysteine and disulfides (N,N-diacetylcysteine and N-acetylcysteine). Cysteine is further metabolized to form glutathione and other metabolites.

Excretion

After a single oral dose of [^35S]-acetylcysteine 100 mg, between 13 to 38% of the total radioactivity administered was recovered in urine within 24 hours. In a separate study, renal clearance was estimated to be approximately 30% of total body clearance.

Specific Populations:

Hepatic Impairment:

Following a 600 mg intravenous dose of acetylcysteine to subjects with mild (Child Pugh Class A, n=1), moderate (Child-Pugh Class B, n=4) or severe (Child-Pugh Class C; n=4) hepatic impairment and 6 healthy matched controls, mean T1/2 increased by 80%. Also, the mean CL decreased by 30% and the systemic acetylcysteine exposure (mean AUC) increased 1.6-fold in subjects with hepatic impairment compared to subjects with normal hepatic function. These changes are not considered to be clinically meaningful.

Renal Impairment

Hemodialysis may remove some of total acetylcysteine.

13 NONCLINICAL TOXICOLOGY

13.1 Carcinogenesis, Mutagenesis, Impairment of Fertility

Long-term studies in animals have not been performed to evaluate the carcinogenic potential of acetylcysteine.

Acetylcysteine was not genotoxic in the Ames test or the in vivo mouse micronucleus test. It was, however, positive in the in vitro mouse lymphoma cell (L5178Y/TK+/-) forward mutation test.

Treatment of male rats with acetylcysteine at an oral dose of 250 mg/kg/day for 15 weeks (0.1 times the recommended total human intravenous dose of 300 mg/kg based on body surface comparison) did not affect the fertility or general reproductive performance.

14 CLINICAL STUDIES

Loading Dose/Infusion Rate Study

A randomized, open-label, multi-center clinical study was conducted in Australia in patients with acetaminophen poisoning to compare the rates of hypersensitivity reactions between two rates of infusion for the intravenous acetylcysteine loading dose. One hundred nine subjects were randomized to a 15-minute infusion rate and seventy-one subjects were randomized to a 60 minute infusion rate. The loading dose was 150 mg/kg followed by a maintenance dose of 50 mg/kg over 4 hours and then 100 mg/kg over 16 hours. Of the 180 patients, 27% were male and 73% were female. Ages ranged from 15 to 83 years, with the mean age being 30 years (±13.0).

A subgroup of 58 subjects (33 in the 15-minute infusion group; 25 in the 60-minute infusion group) was treated within 8 hours of acetaminophen ingestion. No hepatotoxicity occurred within this subgroup; however, with 95% confidence, the true hepatotoxicity rates could range from 0% to 9% for the 15-minute infusion group and from 0% to 12% for the 60-minute infusion group.

Observational Study

An open-label, observational database contained information on 1749 patients who sought treatment for acetaminophen overdose over a 16-year period. Of the 1749 patients, 65% were female, 34% were male and less than 1% was transgender. Ages ranged from 2 months to 96 years, with 72% of the patients falling in the 16 to 40-year-old age bracket. A total of 399 patients received acetylcysteine treatment. A post-hoc analysis identified 56 patients who (1) were at high or probable risk for hepatotoxicity (APAP greater than 150 mg/L at the four hours line according to the Australian nomogram) and (2) had a liver function test. Of the 53 patients who were treated with intravenous acetylcysteine (300 mg/kg intravenous acetylcysteine administered over 20-21 hours) within 8 hours, two (4%) developed hepatotoxicity (AST or ALT greater than 1000 U/L). Twenty-one of 48 (44%) patients treated with acetylcysteine after 15 hours developed hepatotoxicity. The actual number of hepatotoxicity outcomes may be higher than what is reported here. For patients with multiple admissions for acetaminophen overdose, only the first overdose treated with intravenous acetylcysteine was examined. Hepatotoxicity may have occurred in subsequent admissions.

Evaluable data were available from a total of 148 pediatric patients (less than 16 years of age) who were admitted for poisoning following ingestion of acetaminophen, of whom 23 were treated with intravenous acetylcysteine. There were no deaths of pediatric patients. None of the pediatric patients receiving intravenous acetylcysteine developed hepatotoxicity while two patients not receiving intravenous acetylcysteine developed hepatotoxicity. The number of pediatric patients is too small to provide a statistically significant finding of efficacy; however the results appear to be consistent to those observed for adults.

16 HOW SUPPLIED/STORAGE AND HANDLING

Acetylcysteine injection is available as a 20% solution (200 mg/mL) in 30 mL single dose glass vials. Each single dose vial contains 6 g/30 mL (200 mg/mL) of acetylcysteine injection. Acetylcysteine injection is sterile and can be used for intravenous administration. It is available as follows:

- 30 mL vials, carton of 4 (NDC 0574-0805-30)

Do not use previously opened vials for intravenous administration.

Note: The color of acetylcysteine injection may turn from essentially colorless to a slight pink or purple once the stopper is punctured. The color change does not affect the quality of the product.

The stopper in the acetylcysteine injection vial is formulated with a synthetic base-polymer and does not contain Natural Rubber Latex, Dry Natural Rubber, or blends of Natural Rubber.

Store unopened vials at controlled room temperature, 20° to 25°C (68° to 77°F) [See USP Controlled Room Temperature].

17 PATIENT COUNSELING INFORMATION

Hypersensitivity Reactions

Advise patients and caregivers that hypersensitivity reactions related to administration and infusion may occur during and after acetylcysteine injection treatment, including hypotension, wheezing, shortness of breath and bronchospasm [see Warnings and Precautions (5.1)].

For specific treatment information regarding the clinical management of acetaminophen overdose, please contact your regional poison center at 1-800-222-1222, or alternatively, a special health professional assistance line for acetaminophen overdose at 1-800-525-6115.

U.S. Patent Nos. 8,148,356, 8,399,445, 8,653,061 8,722,738 and 9,327,028

Manufactured for Padagis®
Minneapolis, MN 55427
www.padagis.com

Rev 01-24
33U00 RC PH3

Package/Label Display Panel

NDC 0574-0805-30

Rx Only

Acetylcysteine Injection

6 g/30 mL (200 mg/mL)

MUST BE FURTHER DILUTED PRIOR TO INTRAVENOUS USE

4 X 30 mL Sterile Vials